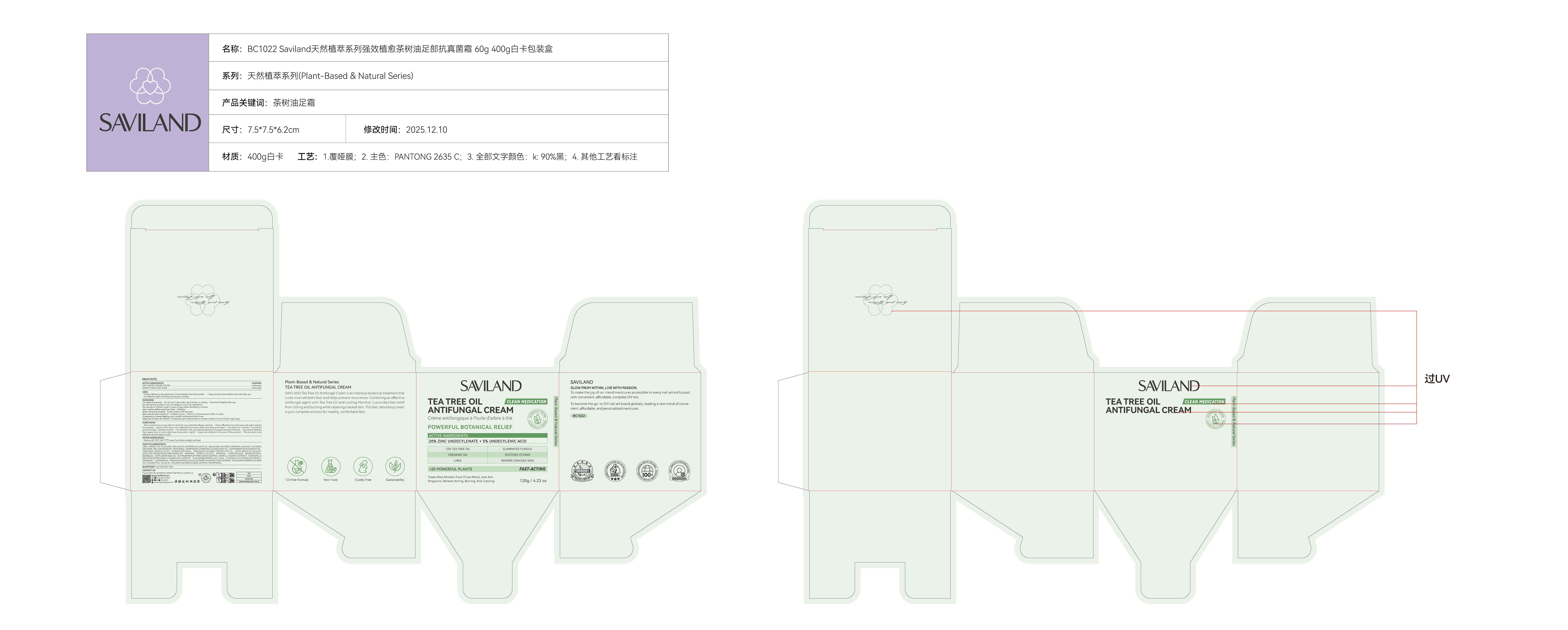 DRUG LABEL: TEA TREE Oil ANTIFUNGAL Cream
NDC: 85966-008 | Form: CREAM
Manufacturer: GUANGZHOU SAWEILAN IMPORT & EXPORT TRADING CO., LTD
Category: otc | Type: HUMAN OTC DRUG LABEL
Date: 20251212

ACTIVE INGREDIENTS: UNDECYLENIC ACID 0.05 g/1 g; ZINC UNDECYLENATE 0.2 g/1 g
INACTIVE INGREDIENTS: WATER; ORIGANUM VULGARE LEAF OIL; GLYCERIN; PEG-100 STEARATE; SIMMONDSIA CHINENSIS (JOJOBA) SEED OIL; PHENOXYETHANOL; C13-15 ALKANE; SQUALANE; EDETATE DISODIUM; OLIVE OIL; TOCOPHEROL; BISABOLOL; BUTYROSPERMUM PARKII (SHEA) BUTTER; CALENDULA OFFICINALIS FLOWER; ALOE VERA LEAF JUICE; MELALEUCA ALTERNIFOLIA (TEA TREE) LEAF OIL; MENTHOL; COCONUT OIL; SOY SPHINGOLIPIDS; CENTELLA ASIATICA TRITERPENOIDS; MACADAMIA TERNIFOLIA SEED OIL; LECITHIN, SUNFLOWER; XANTHAN GUM; SUNFLOWER OIL; PANTHENOL; LAVENDER OIL; CETEARYL ALCOHOL; GLYCERYL STEARATE; LEPTOSPERMUM SCOPARIUM BRANCH/LEAF OIL; ACRYLATES/C10-30 ALKYL ACRYLATE CROSSPOLYMER (60000 MPA.S); CAPRYLYL GLYCOL; ARGININE; MATRICARIA CHAMOMILLA FLOWERING TOP; UREA; ROSEMARY; PRUNUS AMYGDALUS DULCIS (SWEET ALMOND) SEED MEAL

85966-008 TEA TREE OIL ANTIFUNGAL CREAM

ACTIVE INGREDIENT

ZINC UNDECYLENATE 20%
UNDECYLENIC ACID 5%

PURPOSE

Antifungal

INDICATIONS AND USAGE

Proven effective in the treatment of most athlete's foot (tinea pedis)
Helps prevent most athlete's foot with daily use
For effective relilef of itching, buring and eracking

WARNINGS

For external use only.

Do not use if seal under cap is broken or missing.
Close the lid tightly after use.
Do not use this product if you are allergic to any of its ingredients.
Do not use on children under 2 years of age unless directed by a doctor

Ask a doctor before use if you have Diabetes.
When using this product ,Avoid contact with the eyes.

Stop use and ask a doctor if . lrritation occurs There is no improvement within 4 weeks.
lf pregnant or breast feeding, ask a health professional before use.

Keep out of reach of children.
lf swallowed, get medical help or contact a Poison Control Center night away.

DOSAGE AND ADMINISTRATION

. Test a small area on your skin to check for any potential allergic reaction. . Clean affected area with soap and water and dry thoroughly. . Apply a thin layer over affected area twice daily (morning and night). . Use daily for 4 weeks, lf condition persists longer, consult a doctor. * For athlete's foot, pay special attention to spaces between the toes.. To prevent athlete's foot, apply once or twice daily (morning and/or night). . Supervise children in the use of this product. . This product is not effective on the scalp or nails.

INACTIVE INGREDIENT

UREA
WATER
C13-15 ALKANE
MELALEUCA ALTERNIFOLIA LEAF OIL
SQUALANE
GLYCERIN
CETEARYL ALCOHOL
GLYCEROL STEARATE
PEG-100 STEARATE
PANTHENOL
SIMMONDSIA CHINENSIS (JOJOBA) SEED OIL
LEPTOSPERMUM SCOPARIUM OIL
CERAMIDE COMPLEX CLR K
PHENOXYETHANOL
ORIGANUM VULGARE HIRTUM LEAF OIL
ACRYLATES/C10-30 ALKYL ACRYLATE CROSSCOPOLYMER (60000 CP)
ARGININE
CAPRYLYL GLYCOL
MENTHOL
XANTHAN GUM
DISODIUM EDTA
BISABOLOL
SUNFLOWER SEED OIL
BUTYROSPERMUM PARKII (SHEA) BUTTER
CENTELLA ASIATICA EXTRACT
CHAMOMILLA RECUTITA (MATRICARIA) FLOWER/LEAF EXTRACT
ALOE BARBADENSIS LEAF JUICE
CALENDULA OFFICINALIS EXTRACT
ROSEMARY
LAVENDER OIL
PRUNUS AMYGDALUS DULCIS (SWEET ALMOND) FRUIT EXTRACT
MACADAMIA TERNIFOLIA SEED OIL
COCONUT OIL
OLIVE OIL
HELIANTHUS ANNUUS SEED LECITHIN
TOCOPHEROL